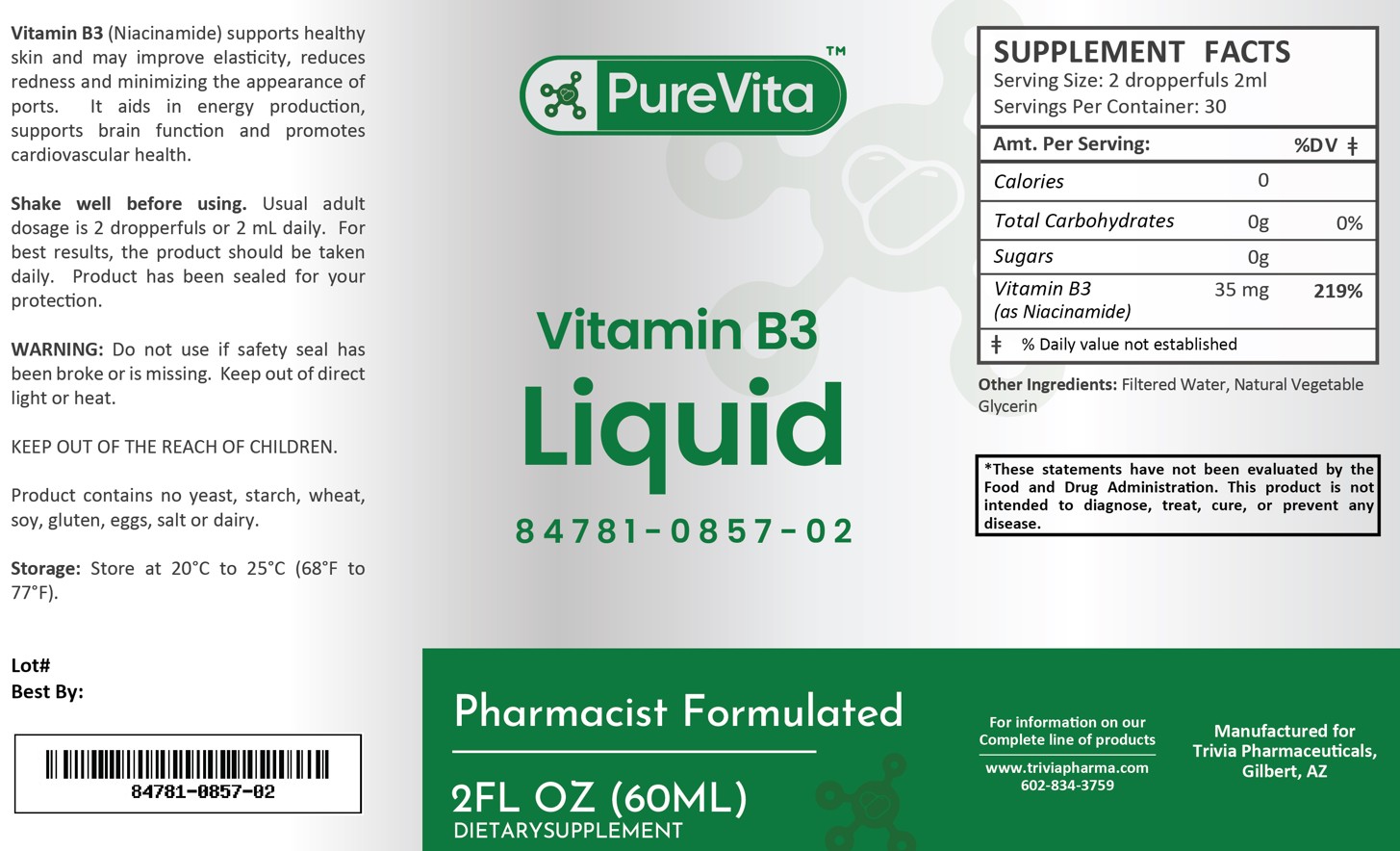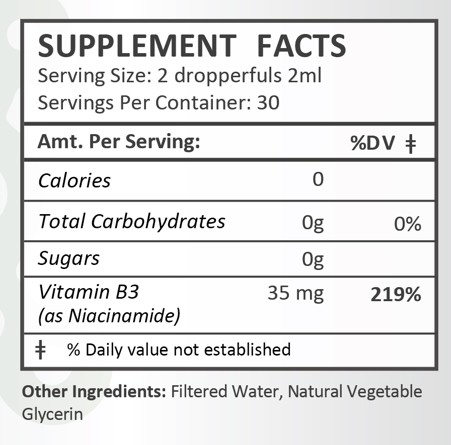 DRUG LABEL: PureVita Vitamin B3
NDC: 84781-857 | Form: LIQUID
Manufacturer: Trivia Pharmaceuticals
Category: other | Type: Dietary Supplement
Date: 20250225

ACTIVE INGREDIENTS: NIACINAMIDE 35 mg/2 mL

PureVita Vitamin B3

Health Claim:

Vitamin B3 35 mg/2 mL Dropper

Description:

PureVita Vitamin B3 (Niacinamide) supports healthy skin and may improve elasticity, reduces redness and minimizing the appearance of pores. It aids in energy production, supports brain function and promotes cardiovascular health.

This listed product is not a National Drug Code, but instead has merely been formatted to comply with standard industry practice for pharmacy and insurance computer systems.

Warnings:

Do not use if safety seal has been broken or is missing. Keep out of direct light or heat.

KEEP OUT OF THE REACH OF CHILDREN.

Product contains no yeast, starch, wheat, soy, gluten, eggs, salt or dairy.

Dosage and Administration:

Usual adult dose is 2 dropperfuls or 2 mL daily. For the best results, the product should be taken daily. Product has been sealed for your protection.

Precautions:

PureVita Vitamin B3 is supplied as clear, white liquid

84781-0857-02

Reserved for Professional Recommendation

All prescriptions using this product shall be pursuant to state statutes as applicable. This is not an Orange Book product. There are no implied or explicit claims on therapeutic equivalence.

Manufactured for:
Trivia Pharmaceuticals

Gilbert, AZ

Storage:

Storage: Store at 20oC to 25oC (68oF to 77oF). Keep refrigerated after opening.